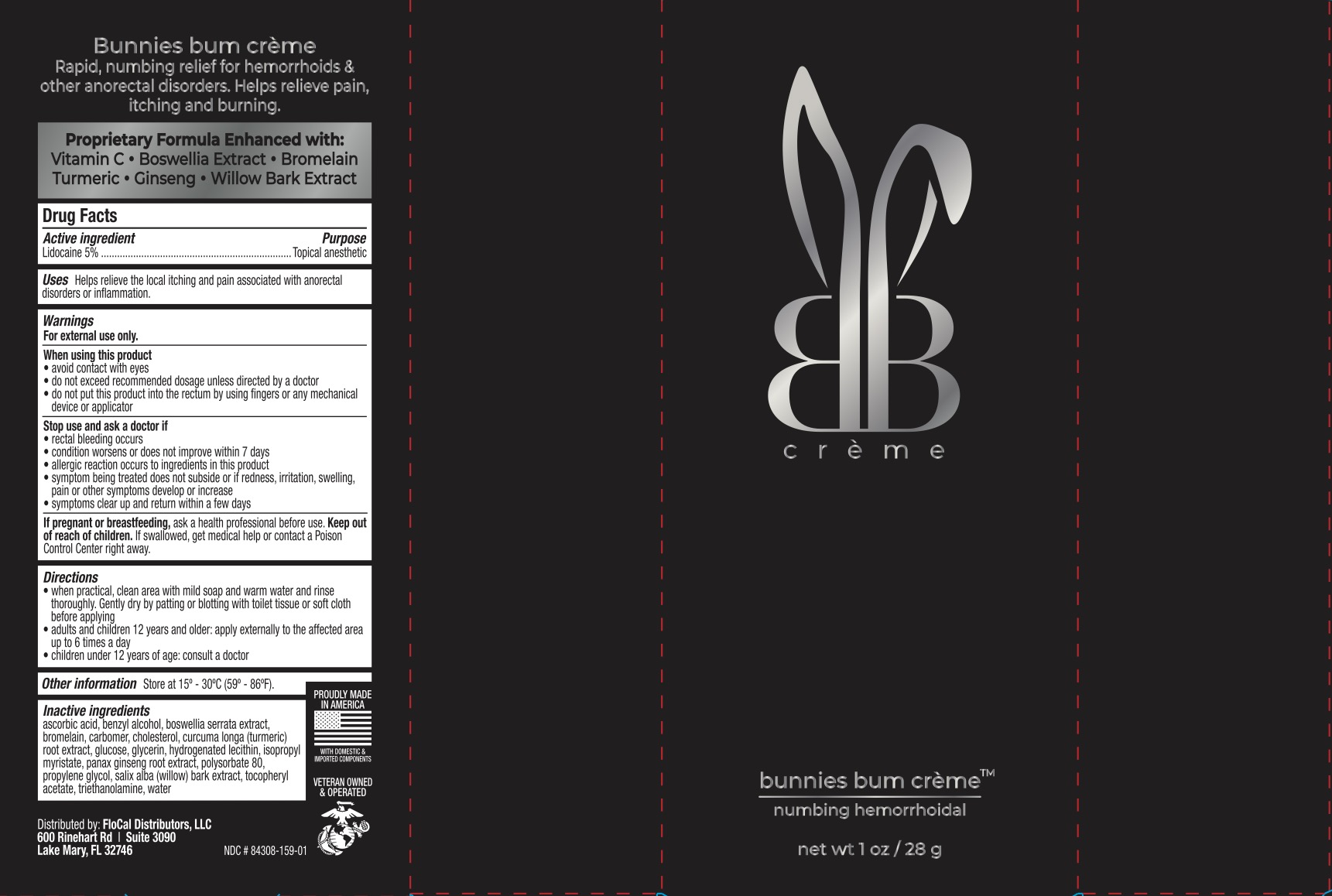 DRUG LABEL: Bunnies Bum Hemorrhoidal Numbing
NDC: 84308-159 | Form: CREAM
Manufacturer: FloCal Distributors LLC
Category: otc | Type: HUMAN OTC DRUG LABEL
Date: 20240705

ACTIVE INGREDIENTS: LIDOCAINE 5 g/100 g
INACTIVE INGREDIENTS: BENZYL ALCOHOL; CARBOMER 940; ANHYDROUS DEXTROSE; .ALPHA.-TOCOPHEROL ACETATE; TURMERIC; GLYCERIN; PROPYLENE GLYCOL; ASIAN GINSENG; POLYSORBATE 80; ISOPROPYL MYRISTATE; WATER; CHOLESTEROL; TROLAMINE; ASCORBIC ACID; INDIAN FRANKINCENSE; BROMELAINS; HYDROGENATED SOYBEAN LECITHIN; SALIX ALBA BARK

ACTIVE INGREDIENT

Lidocaine 5%

PURPOSE

Topical anesthetic

INDICATIONS AND USAGE

Helps relieve the local itching and pain associated with anorectal disorders or inflammation.

WARNINGS

For external use only.

When using this product

- avoid contact with eyes
- do not exceed recommended dosage unless directed by a doctor
- do not put this into the rectum by using fingers or any mechanical device or applicator

Stop use and ask a doctor if

- rectal bleeding occurs
- condition worsens or does not improve within 7 days
- allergic reaction occurs to ingredients in this product
- symptom being treated does not subside or if redness, irritation, swelling, pain or other symptoms develop or increase
- symptoms clear up and return within a few days

PREGNANCY OR BREAST FEEDING

Ask a health professional before use.

KEEP OUT OF REACH OF CHILDREN

If swallowed, get medical help or contact a Poison Control Center right away.

DOSAGE AND ADMINISTRATION

- When practical, clean area with mild soap and warm water and rinse thoroughly. Gently dry by patting or blotting with toilet tissue or soft cloth before applying.
- Adults and children 12 years and older: apply externally to the affected area up to 6 times a day
- Children under 12 years of age: consult a doctor.

INACTIVE INGREDIENT

Ascorbic acid, benzyl alcohol, boswellia serrata extract, bromelain, carbomer, cholesterol, curcuma long (turmeric) root extract, glucose, glycerin, hydrogenated lecithin, isopropyl myristate, panax ginseng root extract, polysorbate 80, propylene glycol, salix alba (willow) bark extract, tocopheryl acetate, triethanolamine, water.